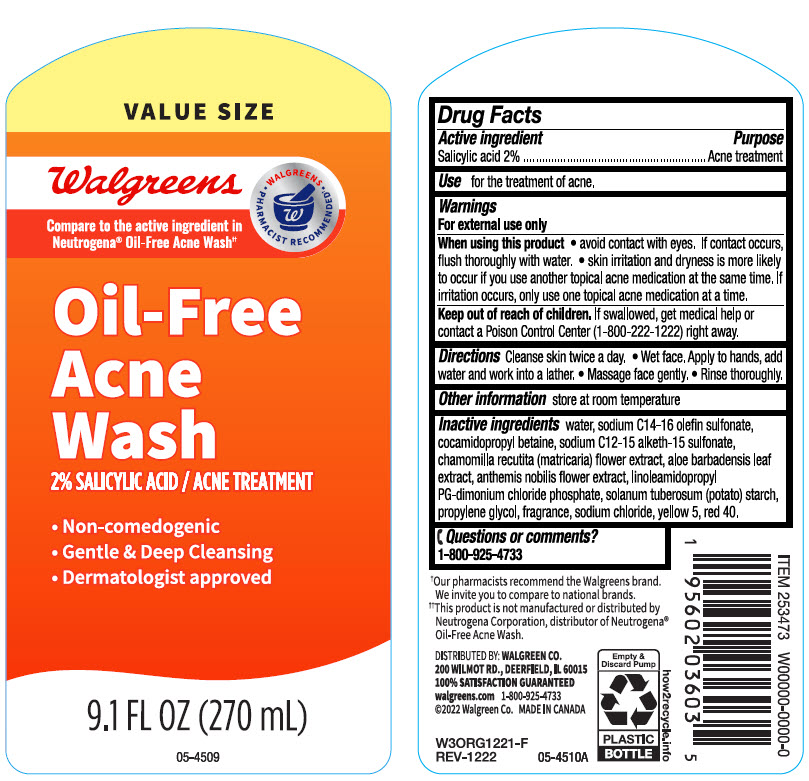 DRUG LABEL: Walgreens Oil-Free Acne Wash
NDC: 0363-3473 | Form: LOTION
Manufacturer: Walgreen Company
Category: otc | Type: HUMAN OTC DRUG LABEL
Date: 20240603

ACTIVE INGREDIENTS: Salicylic Acid 20 mg/1 mL
INACTIVE INGREDIENTS: Water; Sodium C14-16 Olefin Sulfonate; Cocamidopropyl Betaine; Sodium C12-15 Alketh-15 Sulfonate; CHAMOMILE; ALOE VERA LEAF; CHAMAEMELUM NOBILE FLOWER; LINOLEAMIDOPROPYL PROPYLENE GLYCOL-DIMONIUM CHLORIDE PHOSPHATE; STARCH, POTATO; Propylene Glycol; Sodium Chloride; FD&C YELLOW NO. 5; FD&C RED NO. 40

Walgreens Oil-Free Acne Wash
Salicylic Acid

Drug Facts

Active ingredient

Salicylic Acid 2%

Purpose

Acne treatment

Use

for the treatment of acne.

Warnings

For external use only.

When using this product

- avoid contact with eyes. If contact occurs, flush thoroughly with water
- skin irritation and dryness is more likely to occur if you use another topical acne medication at the same time. If irritation occurs, only use one topical acne medication at a time.

Keep out of reach of children. If swallowed, get medical help or contact a Poison Control Center (1-800-222-1222) right away.

Directions

Cleanse skin twice a day.

- Wet face. Apply to hands, add water and work into a lather.
- Massage face gently.
- Rinse thoroughly.

Other information

store at room temperature

Inactive ingredients

water, Sodium C14-16 Olefin Sulfonate, Cocamidopropyl Betaine, Sodium C12-15 Alketh-15 Sulfonate, Chamomille Recutita (Matricaria) Flower Extract, Aloe Barbadensis Leaf Extract, Anthemis Nobilis Flower Extract, Linoleamidopropyl PG-Dimonium Chloride Phosphate, Solanum Tuberosum (Potato) Starch, Propylene Glycol, Fragrance, Sodium Chloride, Yellow 5, Red 40.

Questions or comments?

1-800-925-4733

DISTRIBUTED BY: WALGREEN CO.
200 WILMOT RD., DEERFIELD, IL 60015

PRINCIPAL DISPLAY PANEL - 270 mL Bottle Label

VALUE SIZE

Walgreens

Compare to the active ingredient in
Neutrogena® Oil-Free Acne Wash††

• WALGREENS
PHARMACIST RECOMMENDED†•

Oil-Free
Acne
Wash
2% SALICYLIC ACID / ACNE TREATMENT

- Non-comedogenic
- Gentle & Deep Cleansing
- Dermatologist approved

9.1 FL OZ (270 mL)

05-4509